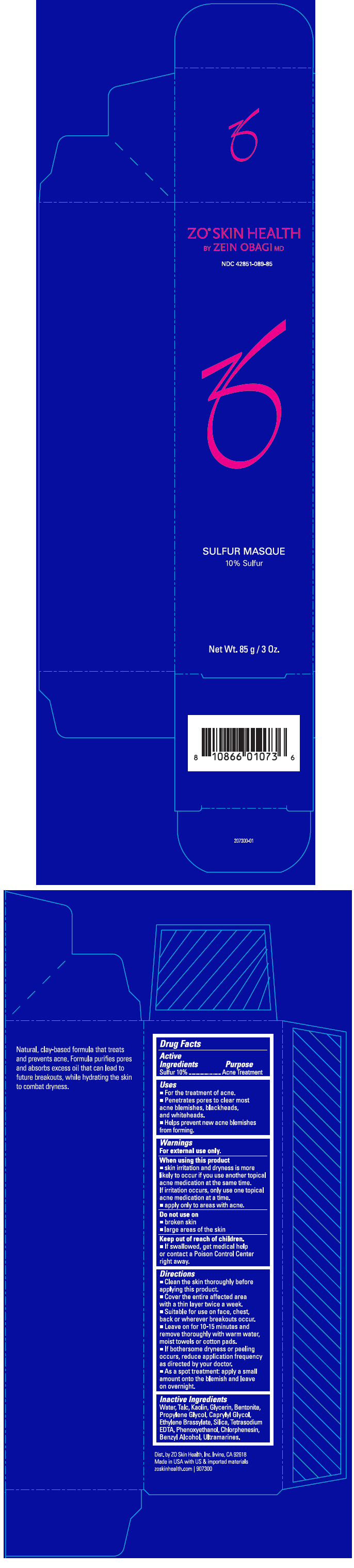 DRUG LABEL: ZO Skin Health Sulfur Masque
NDC: 42851-089 | Form: CREAM
Manufacturer: ZO Skin Health, Inc.
Category: otc | Type: HUMAN OTC DRUG LABEL
Date: 20220509

ACTIVE INGREDIENTS: SULFUR 100 mg/1 g
INACTIVE INGREDIENTS: WATER; TALC; KAOLIN; GLYCERIN; BENTONITE; PROPYLENE GLYCOL; CAPRYLYL GLYCOL; ETHYLENE BRASSYLATE; SILICON DIOXIDE; EDETATE SODIUM; PHENOXYETHANOL; CHLORPHENESIN; BENZYL ALCOHOL; ULTRAMARINE BLUE

ZO® Skin Health Sulfur Masque
National Drug Code 42851-089-85

Drug Facts

Active Ingredients

Sulfur 10%

Purpose

Acne Treatment

Uses

- For the treatment of acne.
- Penetrates pores to clear most acne blemishes, blackheads, and whiteheads.
- Helps prevent new acne blemishes from forming.

Warnings

For external use only.

When using this product

- skin irritation and dryness is more likely to occur if you use another topical acne medication at the same time.
  If irritation occurs, only use one topical acne medication at a time.
- apply only to areas with acne.

Do not use on

- broken skin
- large areas of the skin

Keep out of reach of children.

- If swallowed, get medical help or contact a Poison Control Center right away.

Directions

- Clean the skin thoroughly before applying this product.
- Cover the entire affected area with a thin layer twice a week.
- Suitable for use on face, chest, back or wherever breakouts occur.
- Leave on for 10-15 minutes and remove thoroughly with warm water, moist towels or cotton pads.
- If bothersome dryness or peeling occurs, reduce application frequency as directed by your doctor.
- As a spot treatment: apply a small amount onto the blemish and leave on overnight.

Inactive Ingredients

Water, Talc, Kaolin, Glycerin, Bentonite, Propylene Glycol, Caprylyl Glycol, Ethylene Brassylate, Silica, Tetrasodium EDTA, Phenoxyethanol, Chlorphenesin, Benzyl Alcohol, Ultramarines.

Dist. by ZO Skin Health, Inc. Irvine, CA 92618

PRINCIPAL DISPLAY PANEL - 85 g Tube Carton

ZO® SKIN HEALTH
BY ZEIN OBAGI MD

NDC 42851-089-85

SULFUR MASQUE
10% Sulfur

Net Wt. 85 g / 3 Oz.